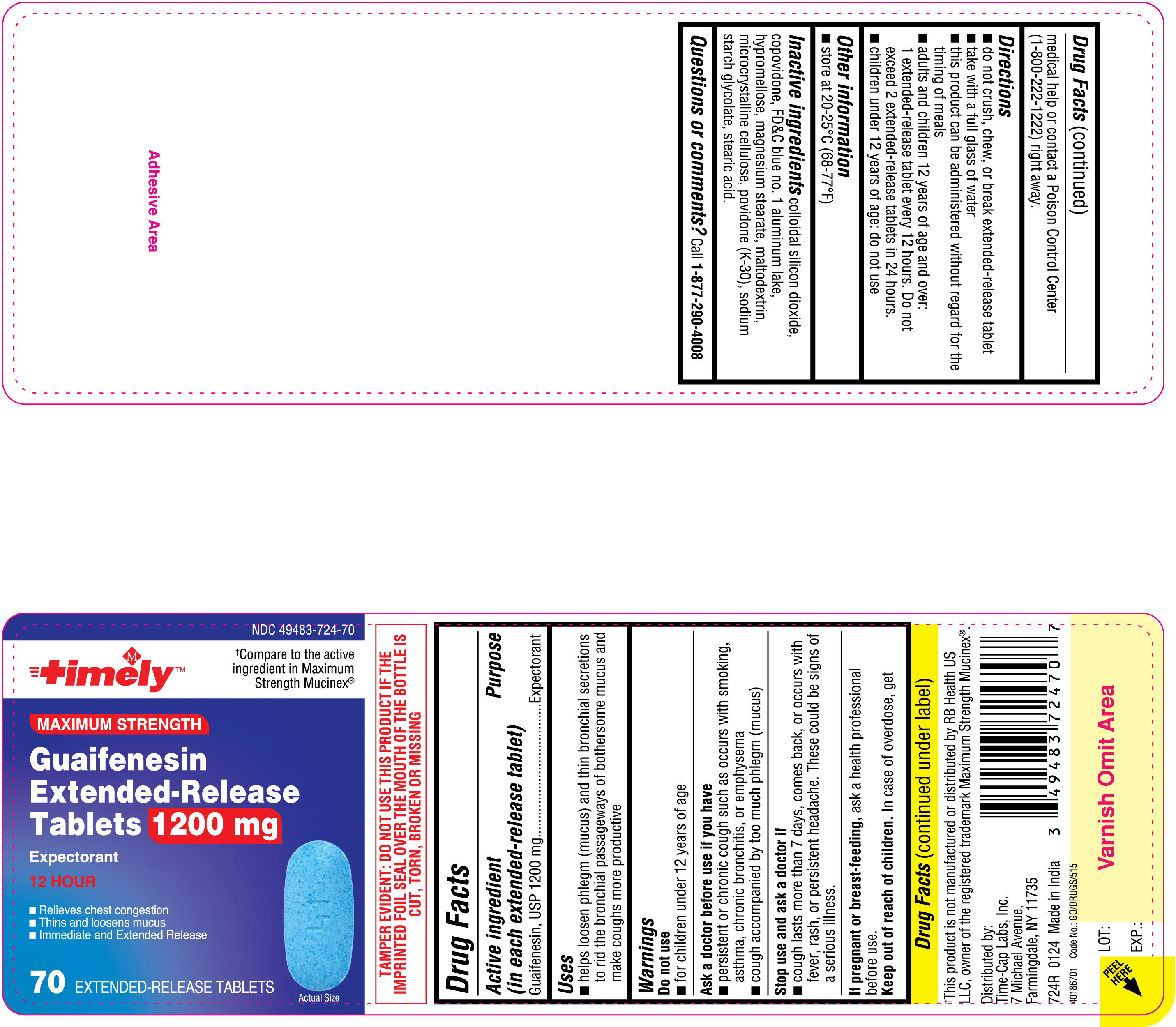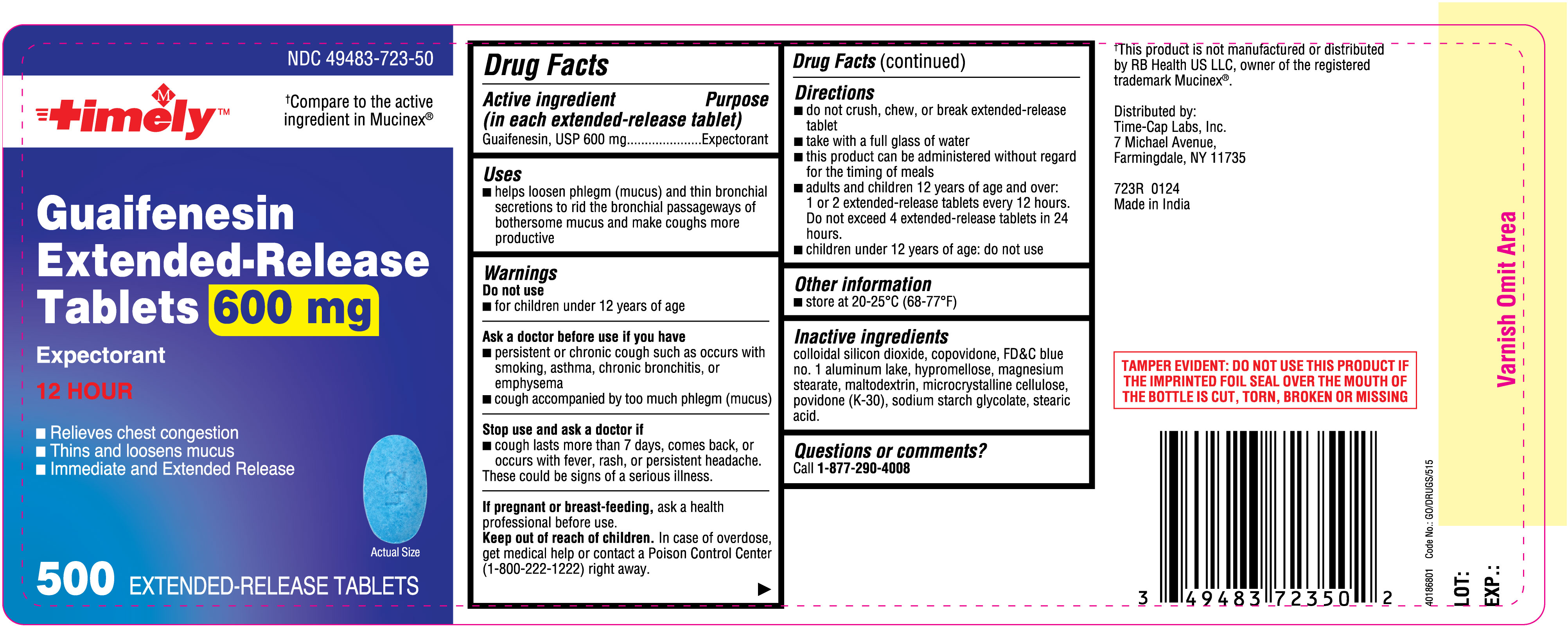 DRUG LABEL: Guaifenesin Extended Release 600 mg
NDC: 49483-723 | Form: TABLET
Manufacturer: TIME CAP LABORATORIES, INC.
Category: otc | Type: HUMAN OTC DRUG LABEL
Date: 20240207

ACTIVE INGREDIENTS: GUAIFENESIN 600 mg/1 1
INACTIVE INGREDIENTS: SILICON DIOXIDE; COPOVIDONE K25-31; HYPROMELLOSE, UNSPECIFIED; MAGNESIUM STEARATE; MALTODEXTRIN; MICROCRYSTALLINE CELLULOSE 102; POVIDONE K30; SODIUM STARCH GLYCOLATE TYPE A; STEARIC ACID; FD&C BLUE NO. 1 ALUMINUM LAKE

Guaifenesin Extended-Release Tablets 600 mg and 1200 mg

OTC - ACTIVE INGREDIENT SECTION

For 600 mg:
Active ingredient (in each extended-release tablet)

Guaifenesin, USP 600 mg

For 1200 mg:
Active ingredient (in each extended-release tablet)

Guaifenesin, USP 1200 mg

OTC - PURPOSE SECTION

Purpose

Expectorant

INDICATIONS & USAGE SECTION

Uses

• helps loosen phlegm (mucus) and thin bronchial secretions to rid the bronchial passageways of bothersome mucus and make coughs more productive

OTC - DO NOT USE SECTION

Do not use

• for children under 12 years of age

OTC - ASK DOCTOR SECTION

Ask a doctor before use if you have

• persistent or chronic cough such as occurs with smoking, asthma, chronic bronchitis, or emphysema
• cough accompanied by too much phlegm (mucus)

OTC - STOP USE SECTION

Stop use and ask a doctor if

- cough lasts more than 7 days, comes back, or occurs with fever, rash, or persistent headache. These could be signs of a serious illness.

OTC - PREGNANCY OR BREAST FEEDING SECTION

If pregnant or breast-feeding,ask a health professional before use.

OTC - KEEP OUT OF REACH OF CHILDREN SECTION

Keep out of reach of children.In case of overdose, get medical help or contact a Poison Control Center (1-800-222-1222) right away.

DOSAGE & ADMINISTRATION SECTION

Directions

For 600 mg

• do not crush, chew, or break extended - release tablet
• take with a full glass of water
• this product can be administered without regard for the timing of meals
• adults and children 12 years of age and over: 1 or 2 extended - release tablets every 12 hours. Do not exceed 4 extended - release tablets in 24 hours.
• children under 12 years of age: do not use

For 1200 mg

• do not crush, chew, or break extended - release tablet
• take with a full glass of water
• this product can be administered without regard for the timing of meals
• adults and children 12 years of age and over: 1 extended - release tablet every 12 hours. Do not exceed 2 extended - release tablets in 24 hours.
• children under 12 years of age: do not use

STORAGE AND HANDLING SECTION

Other information

• store at 20-25°C (68-77°F)

INACTIVE INGREDIENT SECTION

Inactive ingredientscolloidal silicon dioxide, copovidone, FD&C blue No. 1 aluminum lake, hypromellose, magnesium stearate, maltodextrin, microcrystalline cellulose, povidone (K-30), sodium starch glycolate, stearic acid

OTC - QUESTIONS SECTION

Questions or comments? Call 1-877-290-4008